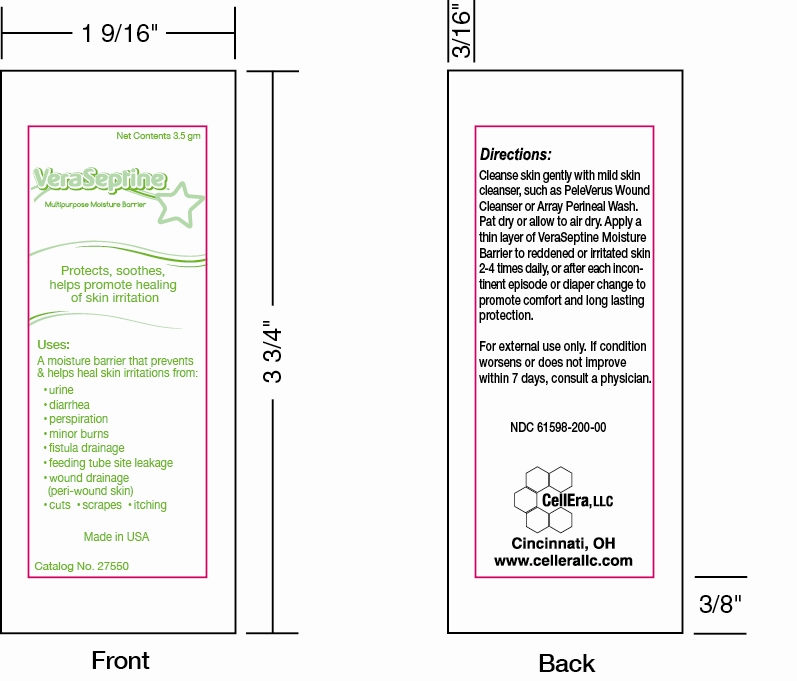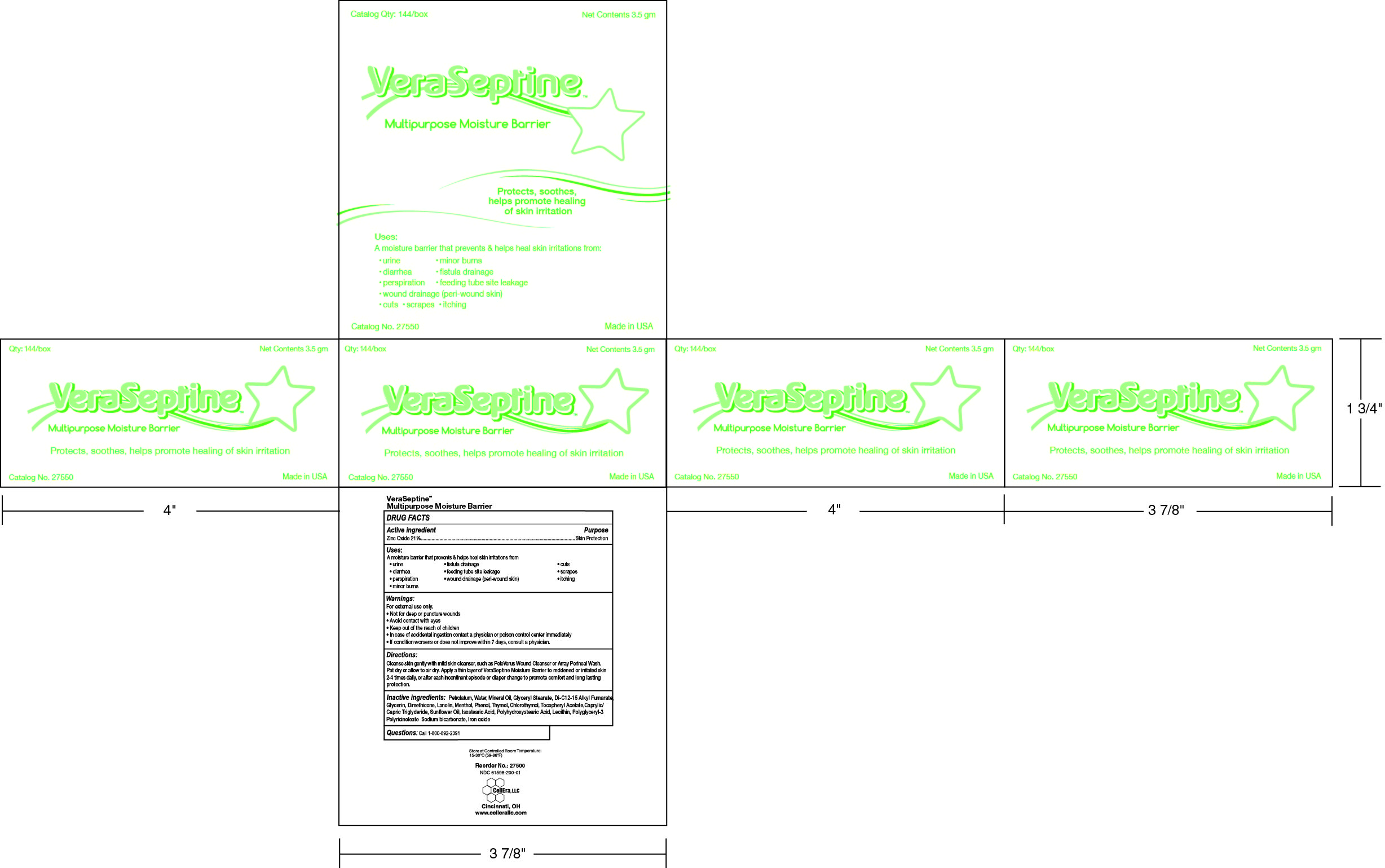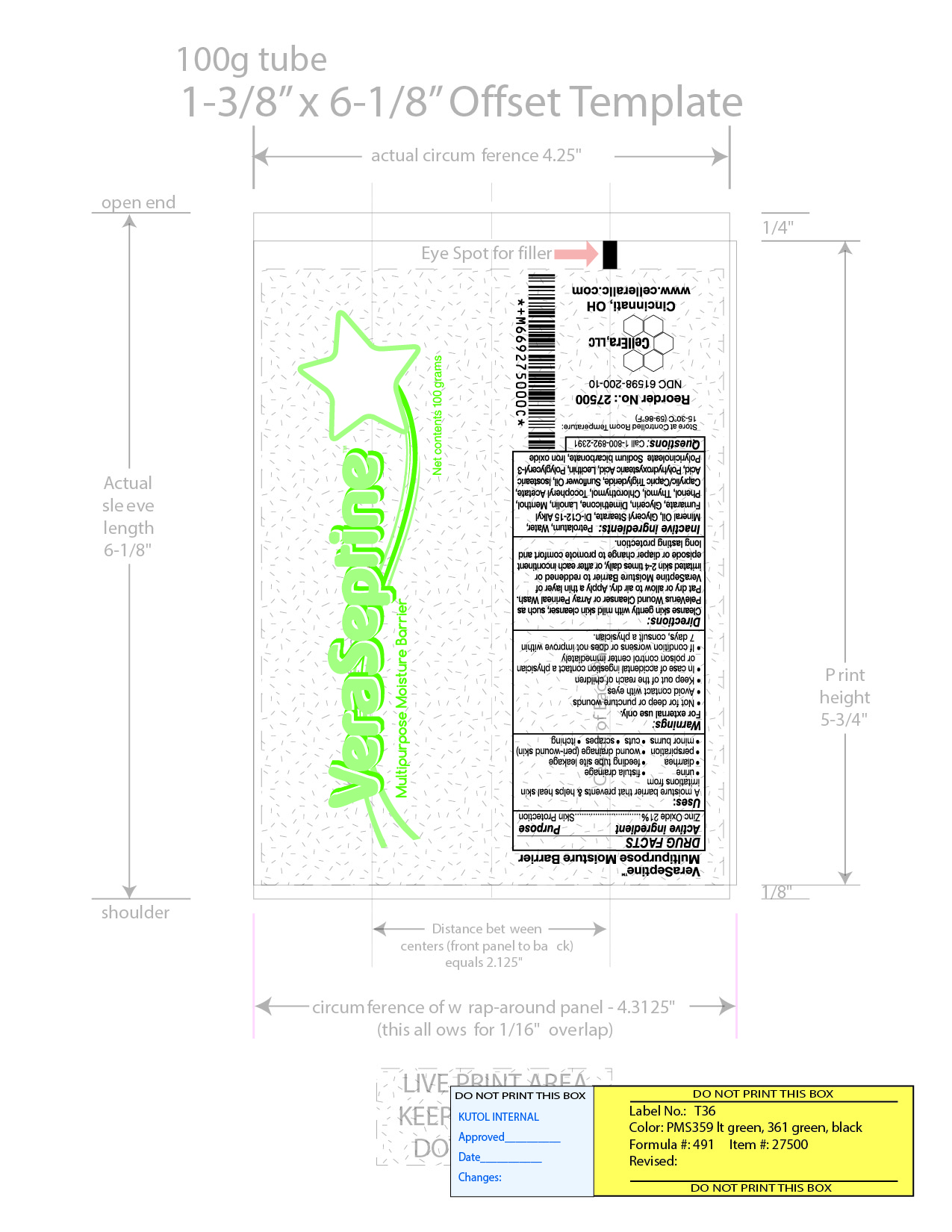 DRUG LABEL: VeraSeptine Multipurpose Moisture Barrier
NDC: 61598-200 | Form: CREAM
Manufacturer: LTC Products, Inc.
Category: otc | Type: HUMAN OTC DRUG LABEL
Date: 20140528

ACTIVE INGREDIENTS: ZINC OXIDE 21 g/100 g
INACTIVE INGREDIENTS: PETROLATUM; MINERAL OIL; DIMETHICONE; GLYCERYL MONOSTEARATE; LANOLIN; MENTHOL; WATER; GLYCERIN; PHENOL; THYMOL; CHLOROTHYMOL; SODIUM BICARBONATE; ALPHA-TOCOPHEROL ACETATE; DI-C12-15 ALKYL FUMARATE

VeraSeptine Multipurpose Moisture Barrier

ACTIVE INGREDIENT

Zinc Oxide 21%....Skin Protection

INACTIVE INGREDIENT

Petrolatum, Water, Mineral Oil, Glyceryl Stearate, Di-C12-15 Alkyl Fumarate, Glycerin, Dimethicone, Lanolin, Menthol, Phenol, Thymol, Chlorothymol, Tocopheryl Acetate, Caprylic/Capric Triglyceride, Sunflower Oil, Isostearic Acid, Polyhydroxystearic Acid, Lecithin, Polyglyceryl-3 Polyricinoleate, Sodium Bicarbonate, Iron Oxide

PURPOSE

A moisture barrier that prevents and helps heal skin irritations from

- Urine
- diarrhea
- perspiration
- minor burns

WARNINGS

For external use only.

- Not for deep or puncture wounds
- Avoid contact with eyes
- Keep out of the reach of children
- In case of accidental ingestion contact a physician or poison control center immediately
- If condition worsens or does not improve within 7 days, consult a physician.

DOSAGE AND ADMINISTRATION

Cleanse skin gently with mild skin cleanser, such as PeleVerus Wound Cleanser or Array Perineal Wash. Pat dry or allow to air dry. Apply a thin layer of VeraSeptine Moisture Barrier to reddened or irritated skin 2-4 times daily, or after each incontinent episode or diaper change to promote comfort and long lasting protection.

INDICATIONS AND USAGE

A moisture barrier that prevents and helps heal skin irritations from urine, diarrhea, perspiration, minor burns, fistula drainage, feeding tube site leakage, wound drainage (peri-wound skin), cuts, scrapes, itching

Avoid contact with the eyes.

Keep out of the reach of children. In case of accidental ingestion contact a physician or poison control center immediately. If condition worsens or does not improve within 7 days, consult a physician.

KEEP OUT OF REACH OF CHILDREN

Keep out of the reach of children. In case of accidental ingestion contact a physician or poison control center immediately

PACKAGE LABEL

61598-200-10.jpg

PACKAGE LABEL

61598-200-00.jpg

PACKAGE LABEL

61598-200-01.jpg